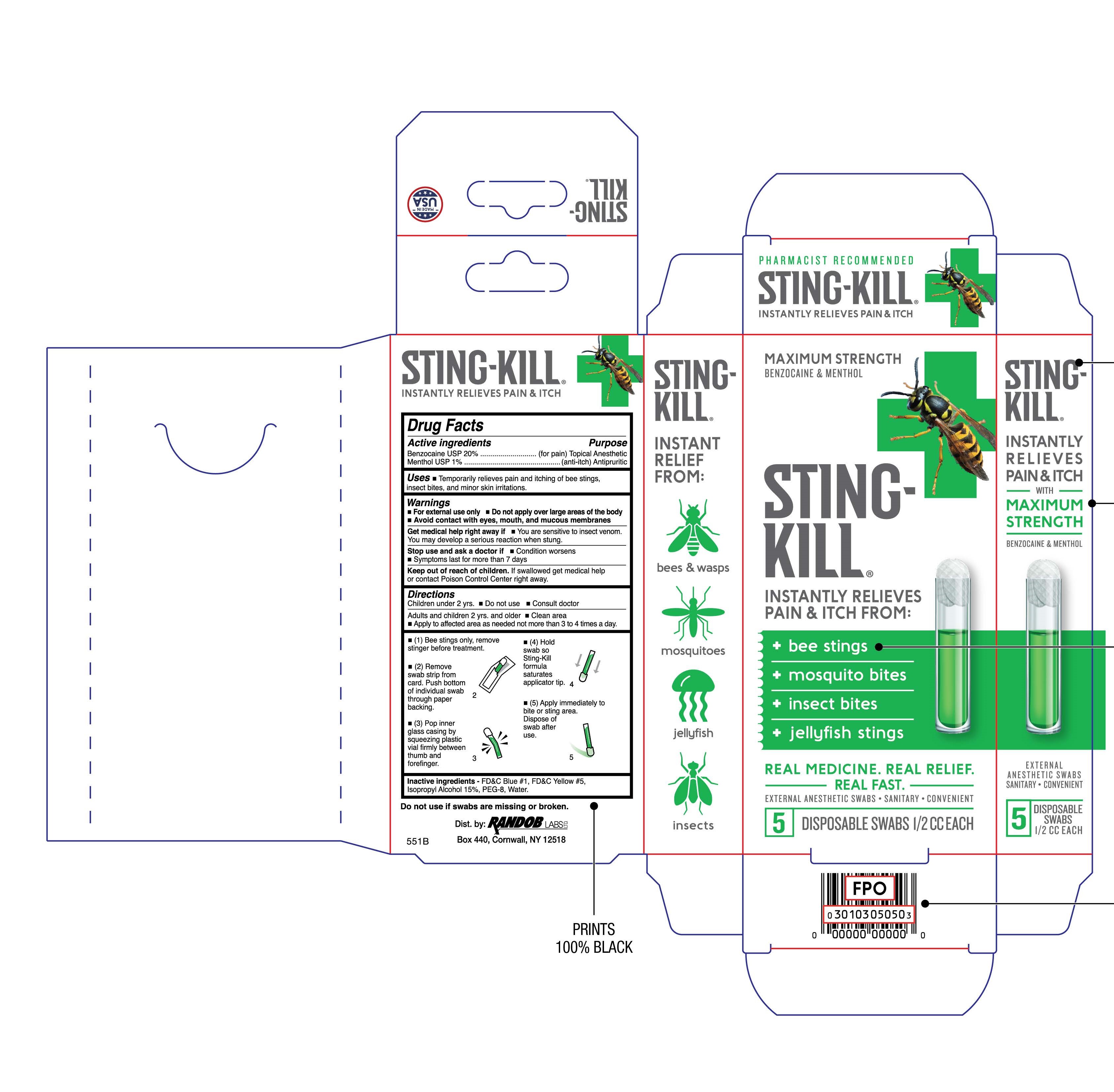 DRUG LABEL: Sting-Kill
NDC: 52412-200 | Form: SOLUTION
Manufacturer: RANDOB LABS, LTD. DBA CROSSINGWELL CONSUMER HEALTH
Category: otc | Type: HUMAN OTC DRUG LABEL
Date: 20231229

ACTIVE INGREDIENTS: BENZOCAINE 200 mg/1 mL; MENTHOL 10 mg/1 mL
INACTIVE INGREDIENTS: FD&C BLUE NO. 1; ISOPROPYL ALCOHOL; PEG-8 LAURATE; WATER

Sting-Kill Swabs

Active ingredients

Benzocaine USP 20%

Menthol USP 1%

Purpose

(for pain) Topical Anesthetic

(anti-itch) Antipruritic

Keep Out of Reach of Children

If swallowed get medical help or contact Poison Control Center right away.

Uses

- Temporarily relieves pain and itching of bee stings, insect bites and minor skin irritations.

Warnings

- For external use only
- Avoid contact with eyes

Get medical help right away if

- You are sensitive to insect venom. You may develop a serious reaction when stung.

Stop use and ask a doctor if

- Condition worsens
- Symptoms last for more than 7 days

Directions

Children under 2 yrs.

- Do not use
- Consult doctor

Adults and children 2 yrs. and older

- Apply to affected area as needed not more than 3 to 4 times a day.
- (1) Bee stings only, remove stinger before treatment.
- (2) Remove strip of swabs from card. Push bottom of individual swab through paper backing.
- (3) Pop inner glass casing by squeezing plastic vial firmly between thumb and forefinger.
- (4) Hold swab so Sting-Kill formula saturates applicator tip.
- (5) Apply immediately to bite or sting area. Dispose of swab after use.

Inactive Ingredients

FD&C Blue #1, FD&C Yellow #5, Isopropyl Alcohol 15%, PEG-8, Water.

Package/Label Principal Display Panel

Maximum Strength

Benzocaine & Menthol

Sting-Kill

Instantly Relieves Paind & Itch From:

bee stings

mosquito bites

insect bites

jellyfish stings

Real Medicine. Real Relief. Real Fast

External Anesthtic Swabs

Sanitary

Convenient

5 Disposable Swabs 1/2 CC Each